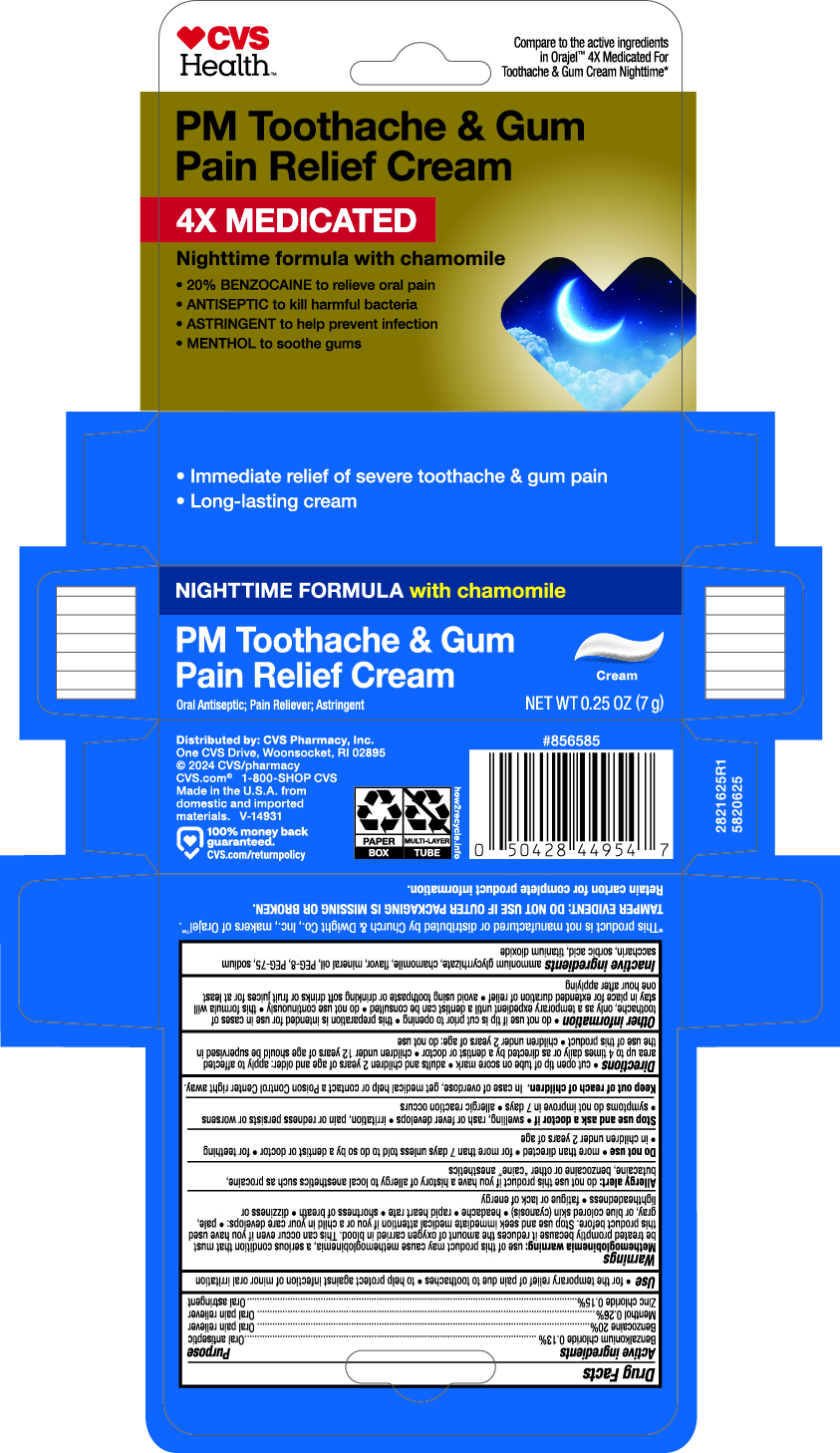 DRUG LABEL: PM Toothache Relief
NDC: 69842-623 | Form: CREAM
Manufacturer: CVS
Category: otc | Type: HUMAN OTC DRUG LABEL
Date: 20251114

ACTIVE INGREDIENTS: BENZOCAINE 20 g/100 g; MENTHOL 0.26 g/100 g; ZINC CHLORIDE 0.15 g/100 g; BENZALKONIUM CHLORIDE 0.13 g/100 g
INACTIVE INGREDIENTS: POLYETHYLENE GLYCOL 400; POLYETHYLENE GLYCOL 3350; AMMONIUM GLYCYRRHIZATE; CHAMOMILE; SORBIC ACID; TITANIUM DIOXIDE; SACCHARIN SODIUM

5820625 CVS Health 4x Medicated Cream PM

DOSAGE AND ADMINISTRATION

For the temporary relief of pain due to toothaches. To help protect aganist infection of minor oral irritation.

INACTIVE INGREDIENT

ammonium glycyrrhizate, chamomile, flavor, mineral oil, PEG-8, PEG-77, sodium saccharin, sorbic acid, titanium dioxide

INDICATIONS AND USAGE

Cut open tip of tube on score mark. Adults and children 2 years of age and older: apply to affected area up to 4 times daily or as directed by a dentist or doctor. Children under 12 years of age should be supervised in the use of this product. Children under 2 years of age: do not use.

ACTIVE INGREDIENT

Belzalkomium Chloride 0.13% Oral antiseptic

Benzocaine 20% Oral pain releiver

Methol 0.26% Oral pain releiver

Zinc chloride 0.15% Oral astringent

Keep out of reach of children. In case of overdose, get medical help or contact a POison Control Center right away.

PURPOSE

Do not nuse if tube tip is cust prior to opening. This preparation is intended for use in cases of toothache, only as a temporary expedient until a dentist can be consulted. Do not use continuously . This formula will stay in place for extended duration of relief. Avoid using toothpaste or drinking soft drinks or fruit juices for at least one hour after applying.

WARNINGS

Methemoglobinemia warning: use of this product may cause methemoglobinemia, a serious condition tha tmust be treated promptly becuase it reduces the amount of oxygen carried in blood. This can occur even if you have used this product before. Stop use and seek immediate medical attention if you or a child in your care develops: pale, gray, or blue colored skin (cyanosis), headache, rapid heart rate, shortness of breath, dizziness or lightheadedness, fatigue or lack of energy.

Principal Display Panel

20% benzocaine to releive oral pain

Kills harmful bacteria

Astringent to help prevent infection

Cools gums and relieves irritation

Net Wt 0.25 oz (7g)